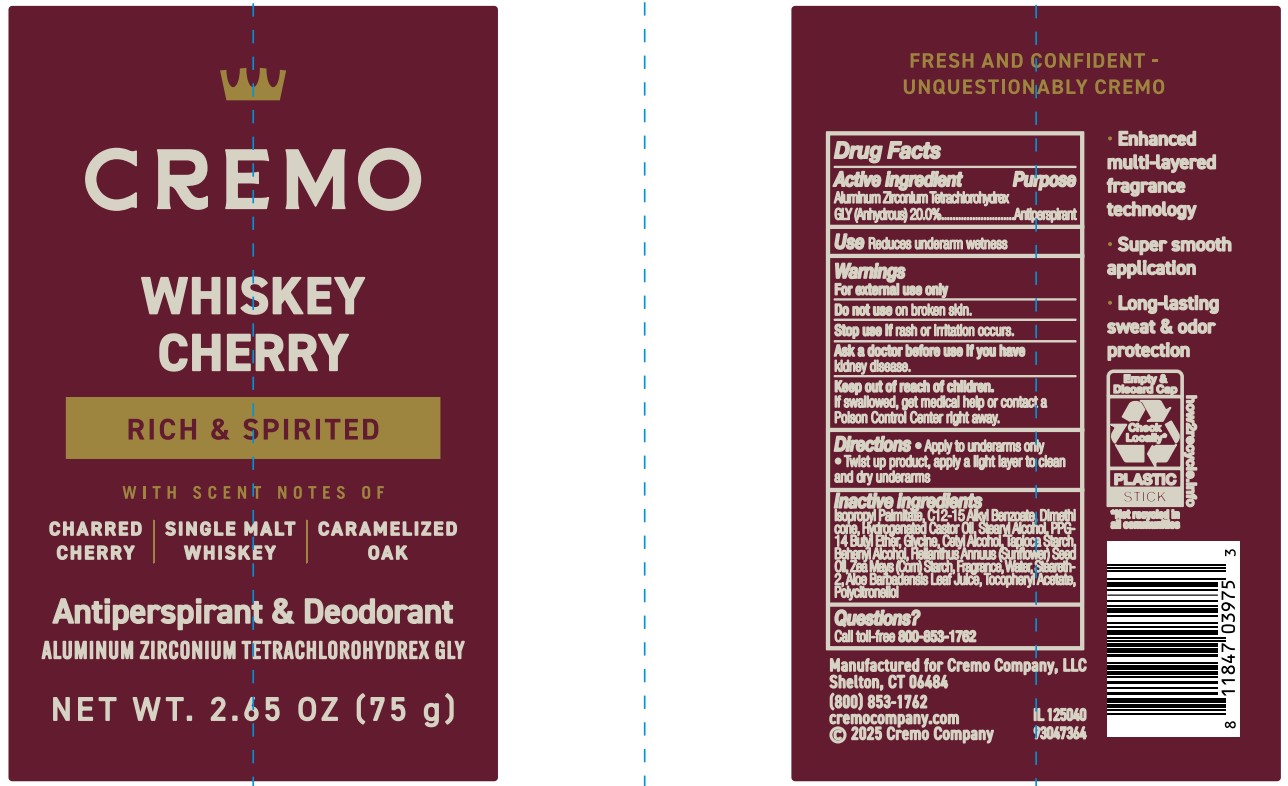 DRUG LABEL: Cremo Company
NDC: 71825-481 | Form: STICK
Manufacturer: Cremo Compay
Category: otc | Type: HUMAN OTC DRUG LABEL
Date: 20260101

ACTIVE INGREDIENTS: ALUMINUM ZIRCONIUM TETRACHLOROHYDREX GLY 20 g/100 mL
INACTIVE INGREDIENTS: ALOE BARBADENSIS LEAF JUICE; PPG-14 BUTYL ETHER; TAPIOCA STARCH; ZEA MAYS (CORN) STARCH; CETYL ALCOHOL; BEHENYL ALCOHOL; WATER; ISOPROPYL PALMITATE; STEARETH-2; C12-15 ALKYL BENZOATE; STEARYL ALCOHOL; .ALPHA.-TOCOPHEROL ACETATE; GLYCINE; HYDROGENATED CASTOR OIL; DIMETHICONE; HELIANTHUS ANNUUS (SUNFLOWER) SEED OIL

Active ingredient

Aluminum Zirconium Tetrachlorohydrex GLY (Anhydrous) 20%

Purpose

Antiperspirant

Use

Reduces underarm wetness

Warnings

For external use only

Do not use

on broken skin.

Stop use if

skin rash or irritation occurs.

Ask a doctor before use if you have

kidney disease.

Keep out of reach of children.

If swallowed, get medical help or contact a Poison Control Center right away.

Directions

• Apply to underarms only. • Twist up product, apply a light layer to clean and dry underarms

Inactive ingredients

Isopropyl Palmitate, C12-15 Alkyl Benzoate, Dimethicone, Hydrogenated Castor Oil, Stearyl Alcohol, PPG-14 Butyl Ether, Glycine, Cetyl Alcohol, Tapioca Starch, Behenyl Alcohol, Helianthus Annuus (Sunflower) Seed Oil, Zea Mays (Corn) Starch, Fragrance, Water, Steareth-2, Aloe Barbadensis Leaf Juice, Tocopheryl Acetate, Polycitronellol.

Questions

Call toll-free 800-853-1762

PACKAGE LABEL

Cremo
WHISKEY CHERRY
RICH & SPIRITED
WITH SCENT NOTES OF
CHARRED CHERRY| SINGLE MALT WHISKEY | CARAMELIZED OAK
Antiperspirant & Deodorant
ALUMINUM ZIRCONIUM TETRACHLOROHYDREX GLY
NET WT. 2.65 OZ (75 g)